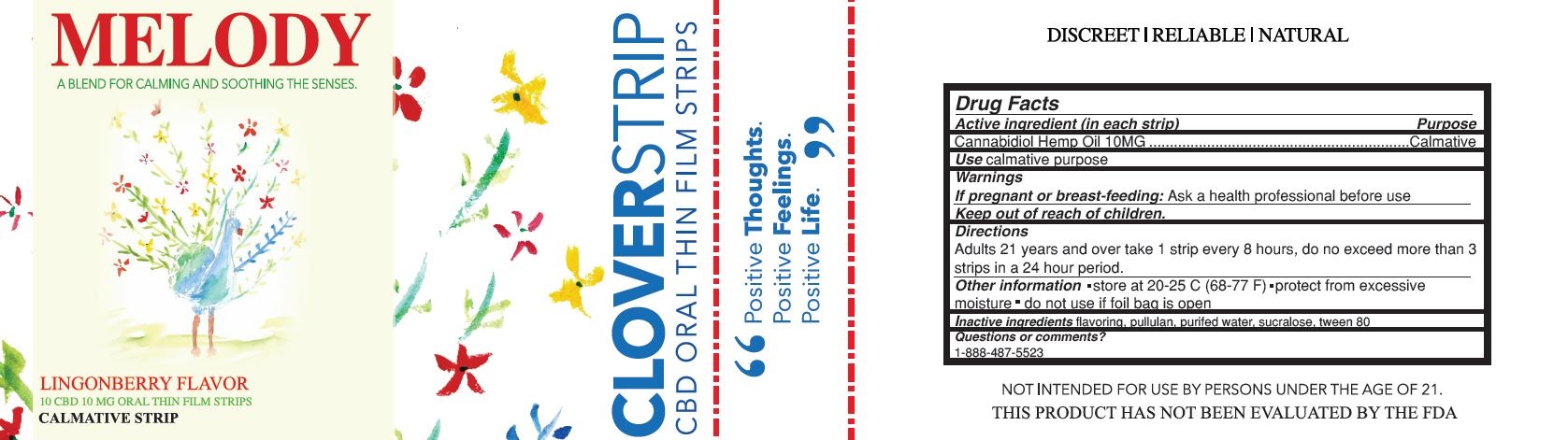 DRUG LABEL: Melody Cloverstrip
NDC: 69305-003 | Form: STRIP
Manufacturer: Advanced Men's Institute
Category: homeopathic | Type: HUMAN OTC DRUG LABEL
Date: 20180622

ACTIVE INGREDIENTS: CANNABIDIOL 10 mg/1 1
INACTIVE INGREDIENTS: PULLULAN; POLYSORBATE 80; WATER; SUCRALOSE

Melody

Active Ingredient (in each strip)

Cannabidiol Hemp Oil 10MG

Purpose

Calmative

Use

calmative purpose

Warnings

If pregnant or breast-feeding: Ask a health professional before use

Keep out of reach of children.

Directions

Adults 21 years and over take 1 strip every 8 hours, do no exceed more than 3 strips in a 24 hour period.

Other Information

• store at 20-25 C (68-77 F) • protect from excessive moisture • do not use if foil bag is open

Inactive Ingredients

flavoring, pullulan, purified water, sucralose, tween 80

PACKAGE LABEL

"Positive Thoughts. Positive Feelings. Positive Life."

DISCREET | RELIABLE | NATURAL

Questions or comments?

1-888-487-5523

NOT INTENDED FOR USE BY PERSONS UNDER THE AGE OF 21.

THIS PRODUCT HAS NOT BEEN EVALUATED BY THE FDA